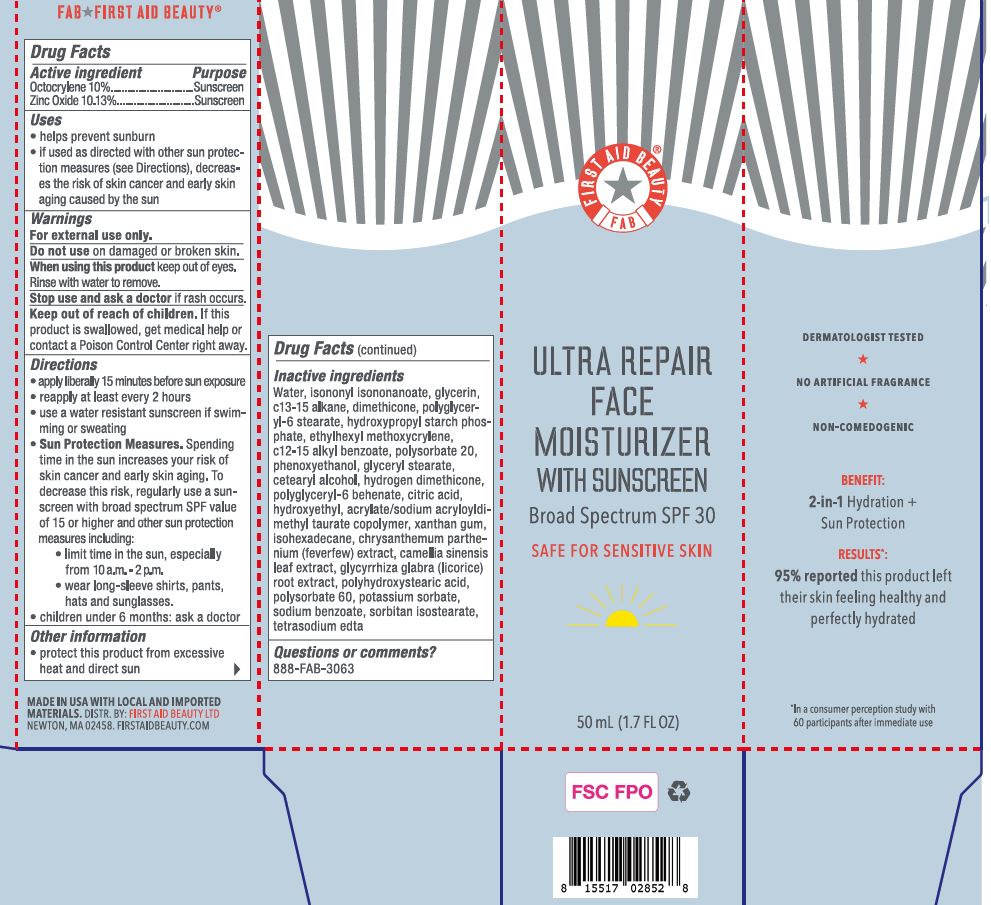 DRUG LABEL: First Aid Beauty FAB Ultra Repair Face Moisturizer with Sunscreen Broad Spectrum SPF 30
NDC: 69423-691 | Form: LOTION
Manufacturer: The Procter & Gamble Manufacturing Company
Category: otc | Type: HUMAN OTC DRUG LABEL
Date: 20251218

ACTIVE INGREDIENTS: OCTOCRYLENE 10 g/100 mL; ZINC OXIDE 10.13 g/100 mL
INACTIVE INGREDIENTS: ISONONYL ISONONANOATE; HYDROXYPROPYL CORN AMYLOPECTIN, PHOSPHATE CROSSLINKED (4000 MPA.S AT 5%); GLYCERIN; C13-15 ALKANE; SODIUM BENZOATE; XANTHAN GUM; WATER; ISOHEXADECANE; GREEN TEA LEAF; ALKYL (C12-15) BENZOATE; CAPRYLYL TRISILOXANE; TANACETUM PARTHENIUM; CITRIC ACID MONOHYDRATE; DIMETHICONE; GLYCYRRHIZA GLABRA; HYDROXYETHYL ACRYLATE/SODIUM ACRYLOYLDIMETHYL TAURATE COPOLYMER (100000 MPA.S AT 1.5%); PHENOXYETHANOL; POLYHYDROXYSTEARIC ACID (2300 MW); EDETATE SODIUM; POLYSORBATE 60; GLYCERYL MONOSTEARATE; CETOSTEARYL ALCOHOL; HYDROGEN DIMETHICONE (13 CST); ETHYLHEXYL METHOXYCRYLENE; POLYGLYCERYL-6 BEHENATE; SORBITAN ISOSTEARATE; POLYSORBATE 20; POLYGLYCERYL-6 STEARATE

First Aid Beauty FAB Ultra Repair Face Moisturizer Broad Spectrum Sunscreen SPF 30

Drug Facts

Active ingredients

Octocrylene 10.0%

Zinc oxide 10.13 %

PURPOSE

Sunscreen

Uses

- helps prevent sunburn
- if used as directed with other sun protection measures (see Directions), decreases the risk of skin cancer and early skin aging caused by the sun

Warnings

For external use only

Do not use

- on damaged or broken skin

When using this product

- keep out of eyes. Rinse with water to remove.

Stop use and ask a doctor if

- rash occurs

Keep out of reach of children. If product is swallowed, get medical help or contact a Poison Control Center right away.

Directions

- apply liberally 15 minutes before sun exposure
- reapply at least every 2 hours
- use water resistant sunscreen if swimming or sweating
- Sun Protection Measures. Spending time in the sun increases your risk of skin cancer and early skin aging. To decrease this risk, regularly use a sunscreen with a Broad Spectrum SPF value of 15 or higher and other sun protection measures including:
  - limit time in sun, especially from 10 a.m. - 2 p.m.
  - wear long-sleeved shirts, pants, hats, and sunglasses
- children under 6 months: ask a doctor

Other information

- protect this product from excessive heat and direct sun

Inactive ingredients

water, isononyl isononanoate, glycerin, c13-15 alkane, dimethicone, polyglyceryl-6 stearate, hydroxypropyl starch phosphate, ethylhexyl methoxycrylene, c12-15 alkyl benzoate, polysorbate 20, phenoxyethanol, glyceryl stearate, cetearyl alcohol, hydrogen dimethicone, polyglyceryl-6 behenate, citric acid, hydroxyethyl acrylate/sodium acryloyldimethyl taurate copolymer, xanthan gum, isohexadecane, chrysanthemum parthenium (feverfew) extract, camellia sinensis leaf extract, glycyrrhiza glabra (licorice) root extract, polyhydroxystearic acid, polysorbate 60, potassium sorbate, sodium benzoate, sorbitan isostearate, tetrasodium edta

Questions?

888-FAB-3063

MADE IN USA.

FIRST AID BEAUTY ® LTD
NEWTON, MA 02458.

WWW.FIRSTAIDBEAUTY.COM

PACKAGE LABEL

First Aid Beauty

FAB

ULTRA REPAIR

FACE

MOISTURIZER

WITH SUNSCREEN

Broad Spectrum

SPF 30

SAFE FOR SENSITIVE SKIN

1.7 FL OZ (50 mL)